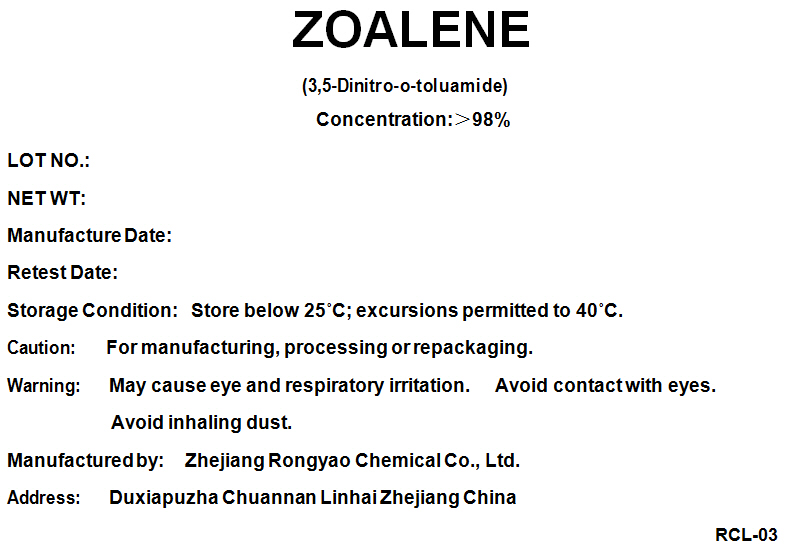 DRUG LABEL: Zoalene
NDC: 67127-003 | Form: POWDER
Manufacturer: Zhejiang Rongyao Biotech Co., Ltd.
Category: other | Type: BULK INGREDIENT - ANIMAL DRUG
Date: 20201019

ACTIVE INGREDIENTS: Dinitolmide 1 kg/1 kg

ZOALENE

PRINCIPAL DISPLAY PANEL - Shipping Label

ZOALENE

(3,5-Dinitro-o-toluamide)

Concentration:>98%

LOT NO.:

NET WT:

Manufacture Date:

Retest Date:

Storage Condition: Store below 25°C; excursions permitted to 40°C.

Caution: For manufacturing, processing or repackaging.

Warning: May cause eye and respiratory irritation. Avoid contact with eyes.
Avoid inhaling dust.

Manufactured by: Zhejiang Rongyao Chemical Co., Ltd.

Address: Duxiapuzha Chuannan Linhai Zhejiang China

RCL-03